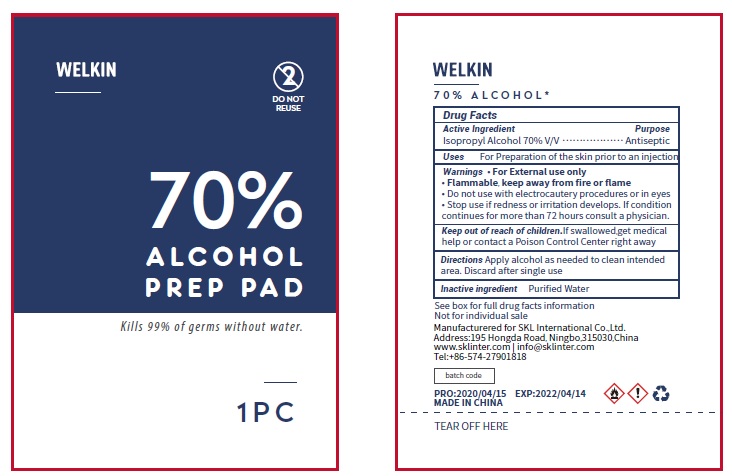 DRUG LABEL: WELKIN Alcohol Prep Pads
NDC: 74542-006 | Form: CLOTH
Manufacturer: Ningbo SKL International Co.,Ltd.
Category: otc | Type: HUMAN OTC DRUG LABEL
Date: 20200427

ACTIVE INGREDIENTS: ISOPROPYL ALCOHOL 0.7 mL/1 1
INACTIVE INGREDIENTS: WATER

Active Ingredient

Isopropyl Alcohol 70% v/v

Purpose

Antiseptic

Uses

For preparation of the skin prior to an injection

Warnings

For external use only
Flammable, keep away from fire or flame
Do not use with electrocautery procedures or in eyes
Stop use if redness or irritation develops. If condition continues for more than 72 hours consult a physician

Keep out of reach of children

If swallowed, get medical help or contact a Poison Control Center right away

Directions

Apply alcohol as needed to clean intended area. Discard after single use.

Inactive ingredients

Purified water